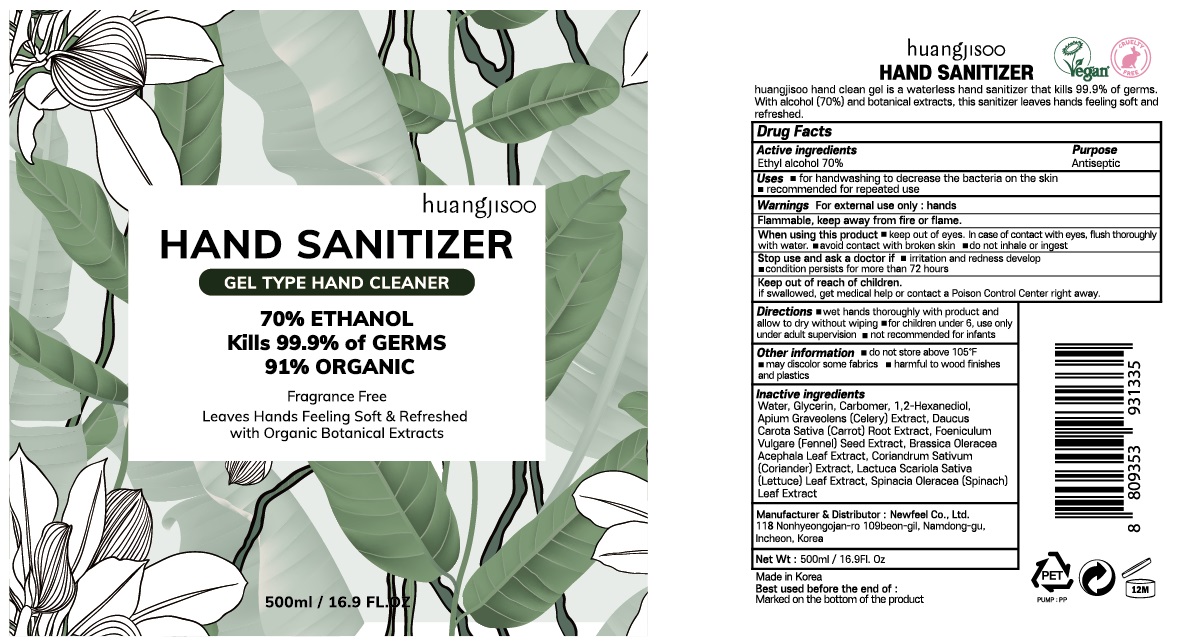 DRUG LABEL: HUANGJISOO HAND SANITIZER
NDC: 73713-030 | Form: GEL
Manufacturer: Newfeel
Category: otc | Type: HUMAN OTC DRUG LABEL
Date: 20200422

ACTIVE INGREDIENTS: ALCOHOL 350 mL/500 mL
INACTIVE INGREDIENTS: Water; Glycerin; CARBOMER HOMOPOLYMER, UNSPECIFIED TYPE; 1,2-Hexanediol; CELERY; CARROT; FENNEL SEED; KALE; CORIANDER; LETTUCE; SPINACH

ACTIVE INGREDIENT

Active ingredients: Ethyl Alcohol 70%

INACTIVE INGREDIENT

Inactive ingredients:

Water, Glycerin, Carbomer, 1,2-Hexanediol, Apium Graveolens (Celery) Extract, Daucus Carota Sativa (Carrot) Root Extract, Foeniculum Vulgare (Fennel) Seed Extract, Brassica Oleracea Acephala Leaf Extract, Coriandrum Sativum (Coriander) Extract, Lactuca Scariola Sativa (Lettuce) Leaf Extract, Spinacia Oleracea (Spinach) Leaf Extract

PURPOSE

Purpose: Antiseptic

WARNINGS

For external use only : hands
Flammable, keep away from fire or flame.
When using this product ■ keep out of eyes. In case of contact with eyes, flush thoroughly with water. ■ avoid contact with broken skin. ■ do not inhale or ingest
Stop use and ask a doctor if ■irritation and redness develop ■ condition persists for more than 72 hours
Keep out of reach of children.
If swallowed, get medical help or contact a Poison Control Center right away.

KEEP OUT OF REACH OF CHILDREN

If swallowed, get medical help or contact a Poison Control Center right away.

Uses

■ for handwashing to decrease the bacteria on the skin
■ recommended for repeated use

Directions

■ wet hands thoroughly with product and allow to dry without wiping

■ for children under 6, use only under adult supervision

■ not recommended for infants

Other information

■ do not store above 105℉

■ may discolor some fabrics

■ harmful to wood finishes and plastics